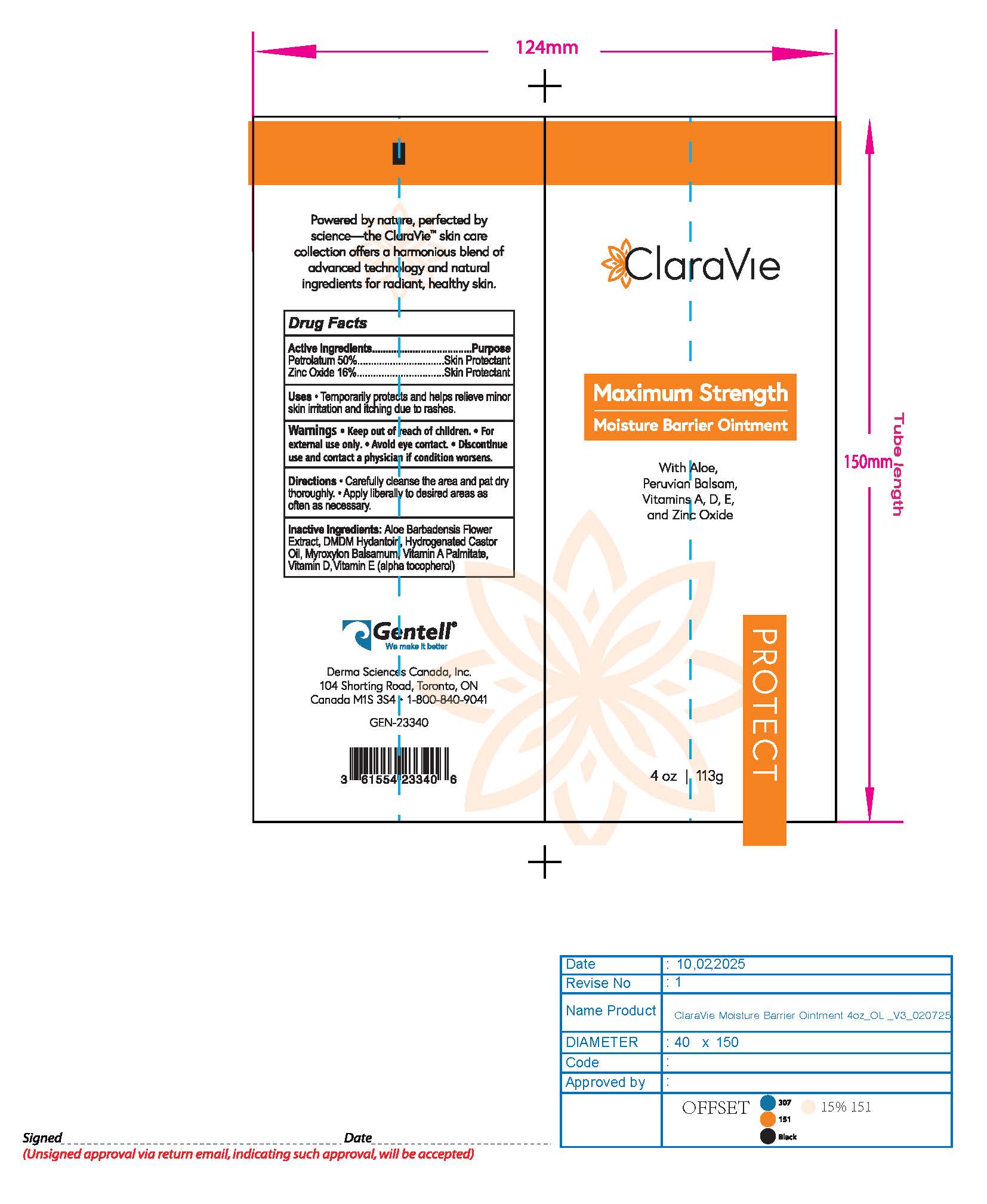 DRUG LABEL: Maximum Strength Moisture Barrier
NDC: 64772-203 | Form: OINTMENT
Manufacturer: Derma Sciences Canada Inc.
Category: otc | Type: HUMAN OTC DRUG LABEL
Date: 20251024

ACTIVE INGREDIENTS: PETROLATUM 0.5 g/1 g; ZINC OXIDE 0.16 g/1 g
INACTIVE INGREDIENTS: ALOE BARBADENSIS LEAF JUICE; VITAMIN D; MYROXYLON BALSAMUM WHOLE; .ALPHA.-TOCOPHEROL ACETATE, D-; DMDM HYDANTOIN; VITAMIN A PALMITATE; HYDROGENATED CASTOR OIL

Maximum Strength Moisture Barrier Ointment

ACTIVE INGREDIENT

Petrolatum 50%

Zinc Oxide 16%

ASK DOCTOR

Discontinue use and contact a physician if condition worsens.

Uses

Temporarily protects and helps relieve minor skin irritation and itching due to rashes

Directions

- Carefully cleanse the area and pat dry thoroughly. Apply liberally to desired areas as often as necessary.

Warnings

Keep out of reach of children. For external use only. Avoid Eye contact. Discontinue use and contact a physician if condition worsens.

INACTIVE INGREDIENT

Aloe Barbadensis Flower Extract, DMDM Hydantoin; Hydrogenated Castor Oil; Myroxylon Balsamum, Vitamin A Palminate, Vitamin D, Vitamin E (Alpha Tocopherol)

PURPOSE

Skin Protectant

Keep out of reach of children

QUESTIONS

1-800-840-9041